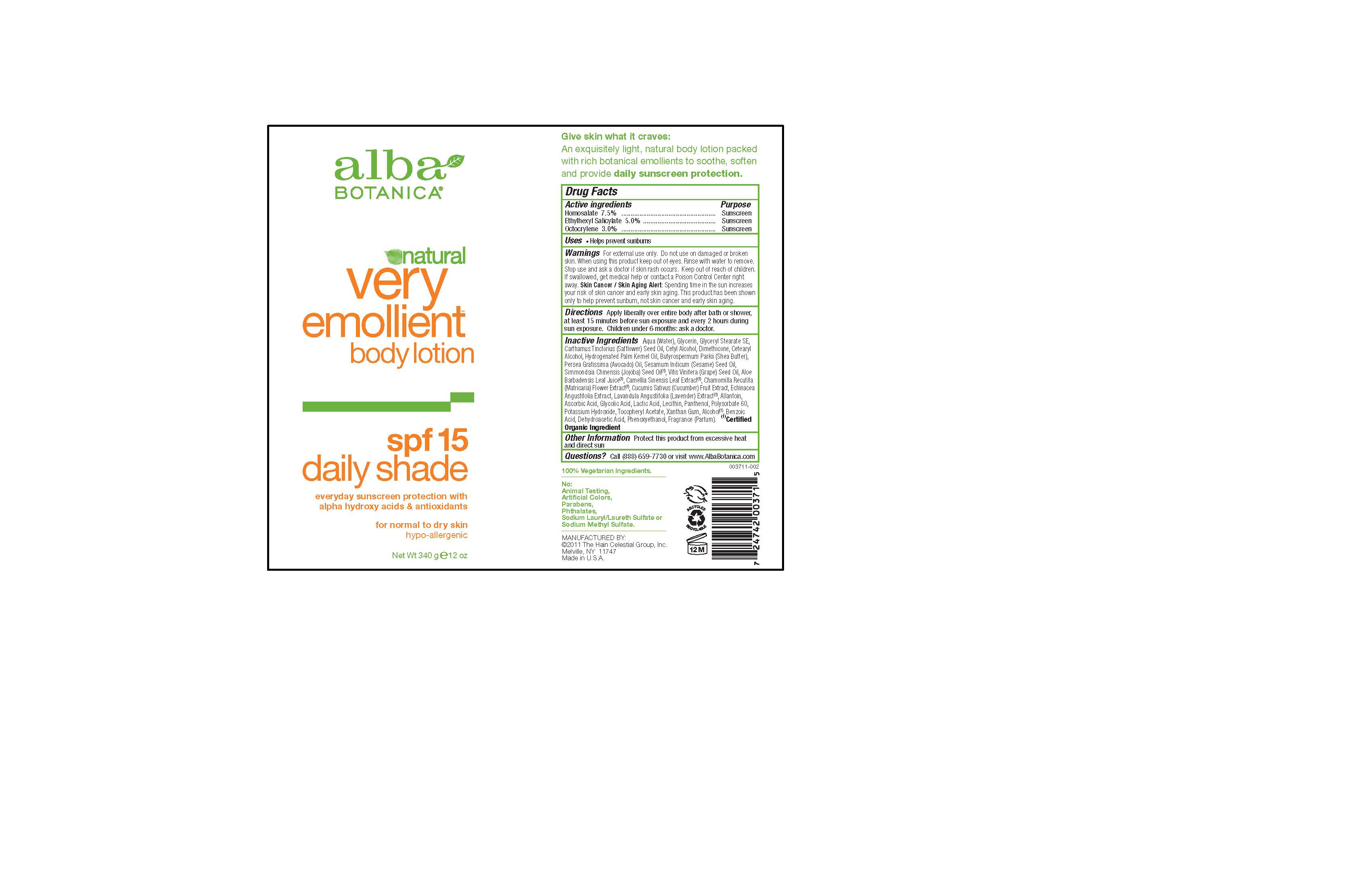 DRUG LABEL: Alba Botanica Natural Very Emollient Daily Shade SPF15
NDC: 61995-2371 | Form: LOTION
Manufacturer: The Hain Celestial Group, Inc.
Category: otc | Type: HUMAN OTC DRUG LABEL
Date: 20120426

ACTIVE INGREDIENTS: HOMOSALATE 7.5 g/100 g; OCTISALATE 5.0 g/100 g; OCTOCRYLENE 3.0 g/100 g
INACTIVE INGREDIENTS: WATER; MEDIUM-CHAIN TRIGLYCERIDES; GLYCERIN; GLYCERYL MONOSTEARATE; SAFFLOWER OIL; CETYL ALCOHOL

Drug Facts

ACTIVE INGREDIENT

Homosalate 7.5%

Ethylhexyl Salicylate 5.0

Octocrylene 3.0%

PURPOSE

Sunscreen

INDICATIONS AND USAGE

- Helps prevent sunburns

WARNINGS

For external use only. Do not use on damaged or broken skin. When using this product keep out of eyes.Rinse with water to remove. Stop use and ask a doctor if skin rash occurs.

Keep out of reach of children. If swallowed, get medical help or contact a Poison Control Center right away.

DOSAGE AND ADMINISTRATION

Apply liberally over entire body after bath or shower, at least 15 minutes before sun exposure and every 2 hours during sun exposure. Children under 6 months ask a doctor.

INACTIVE INGREDIENT

Aqua (Water), Caprylic/Capric Triglyceride, Glycerin, Glyceryl Stearate SE, Carthamus Tinctorius (Safflower) Oil, Cetearyl Alcohol, Hydrogenated Palm Kernel Oil, Butyrospermum Parkii (Shea Butter), Persea Gratissima (Avocado) Oil, Sesamum Indicum (Sesame) Seed Oil, Simmondsia Chinensis (Jojoba) Seed Oil (1), Vitus Vinifera (Grape) Seed Oil, Aloe Barbadensis Leaf Juice (1), Camellia Sinenensis Leaf Extract (1), Chamomilla Recutita (Matricaria) Flower Extract (1), Cucumus Sativus (Cucumber) Fruit Extract, Echinacea Angustifolia Extract, Lavandula Angustifolia (Lavender) Extract (1), Allantoin, Ascorbic Acid, Glycolic Acid, Lactic Acid, Lecithin, Panthenol, Polysorbate 60, Potassium Hydroxide, Tocopheryl Acetate, Alcohol (1), Xanthan Gum, Benzoic Acid, Dehydroacetic Acid, Phenoxyethanol, Fragrance (Parfum)

(1) Certified Organic Ingredients

QUESTIONS

Questions? Call (888) 659-7730 or visit www.AlbaBotanica.com